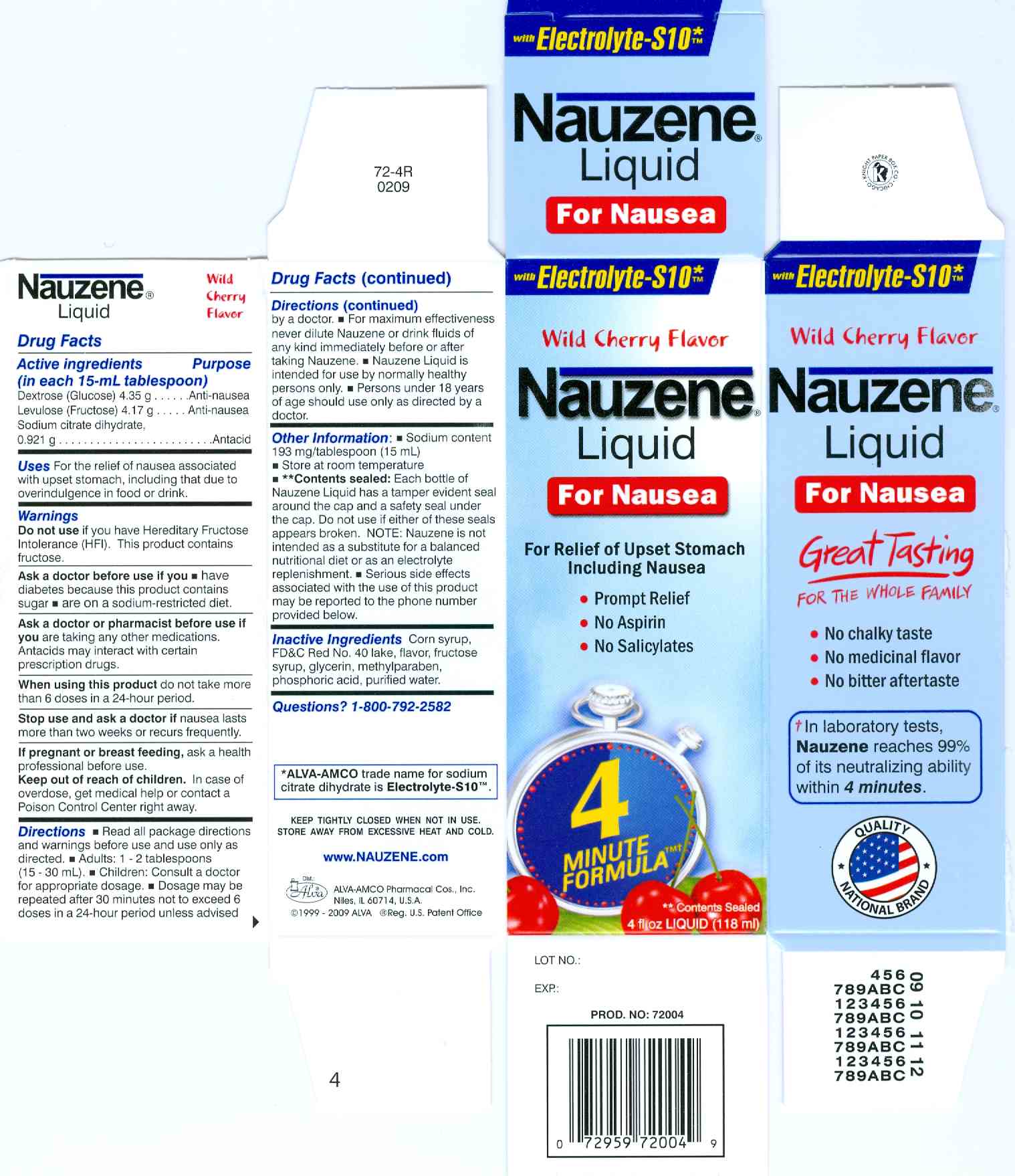 DRUG LABEL: Nauzene
NDC: 52389-172 | Form: SYRUP
Manufacturer: Alva-Amco Pharmacal Companies, Inc.
Category: otc | Type: HUMAN OTC DRUG LABEL
Date: 20100507

ACTIVE INGREDIENTS: TRISODIUM CITRATE DIHYDRATE .921 g/15 mL; Dextrose 4.35 g/15 mL; Fructose 4.17 g/15 mL
INACTIVE INGREDIENTS: corn syrup; FD&C Red No. 40; High fructose corn syrup; Glycerin; Methylparaben; Phosphoric acid; Water

Drug Facts

Active ingredients (in each 15-mL tablespoon)

Dextrose (glucose) 4.35 g...........................anti-nausea

Levulose (fructose) 4.17 g...........................anti-nausea

Sodium citrate dihydrate, 0.921 g................antacid

Uses

For the relief of nausea associated with upset stomach, including that due to overindulgence in food or drink.

Do not use if you have Hereditary Fructose Intolerance (HFI). This product contains fructose.

Ask a doctor before use if you

- you have diabetes because this product contains sugar
- are on a sodium-restricted diet.

Ask a doctor or pharmacist before use if you are taking any other medications. Antacids may interact with certain prescription drugs.

When using this product do not take more than 6 does in a 24-hour period.

Stop use and ask a doctor if nausea lasts more than two weeks or recurs frequently.

PREGNANCY OR BREAST FEEDING

If pregnant or breastfeeding, ask a health professional before use.

Keep out of reach of children. In case of overdose, get medical help or contact a Poison Control Center right away.

Directions

- Read all package directions and warnings before use and use only as directed.
- Adults: 1 - 2 tablespoons (15 - 30 mL).
- Children: Consult a doctor for appropriate dosage.
- Dosage may be repeated after 30 minutes not to exceed 6 doses in a 24-hour period unless advised by a doctor.
- For maximum effectiveness never dilute Nauzene or drink fluids of any kind immediately before or after taking Nauzene.
- Nauzene Liquid is intended for use by normally healthy persons only.
- Persons under 18 years of age should use only as directed by a doctor.

Other information

- Sodium content 193 mg/tablespoon (15 mL).
- Store at room temperature.
- ** Contents sealed: Each bottle of Nauzene Liquid has a tamper evident seal around the cap and a safety seal under the cap. Do not use if either of these seals appears broken. NOTE: Nauzene is not intended as a substitute for a balanced nutritional diet or as an electrolyte replenishment.
- Serious side effects associated with the use of this product may be reported to the phone number provided below.

Inactive ingredients

Corn syrup, FDC Red No. 40 lake, flavor, fructose syrup, glycerin, methylparaben, phosphoric acid, purified water.

Questions? 1-800-792-2582